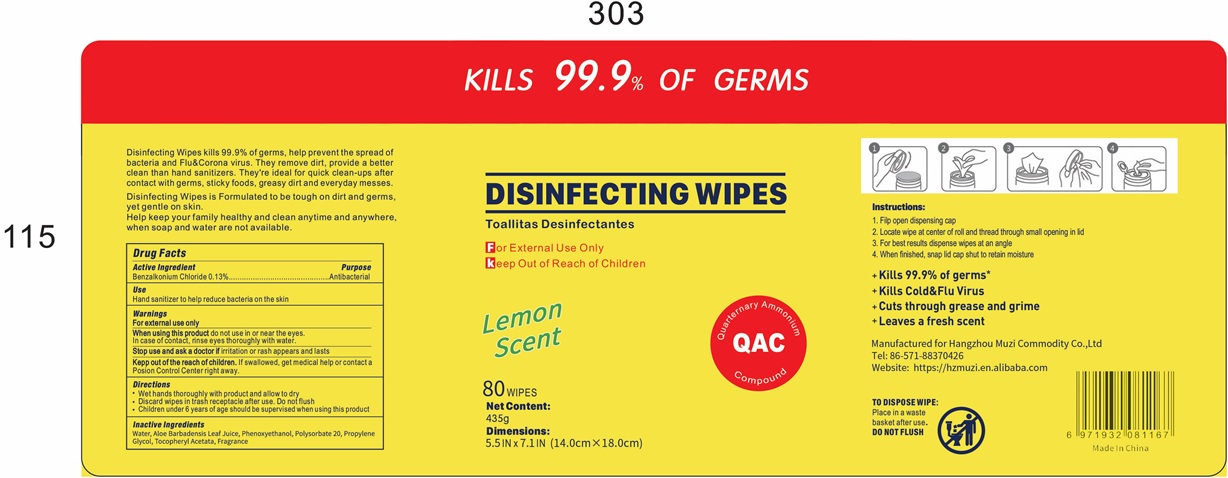 DRUG LABEL: DISINFECTING WIPES
NDC: 80707-201 | Form: CLOTH
Manufacturer: Hangzhou Muzi Commodity Co., Ltd
Category: otc | Type: HUMAN OTC DRUG LABEL
Date: 20201217

ACTIVE INGREDIENTS: BENZALKONIUM CHLORIDE 0.0052 mg/1 1
INACTIVE INGREDIENTS: ALOE VERA LEAF; FRAGRANCE LAVENDER & CHIA F-153480; WATER; POLYSORBATE 20; PHENOXYETHANOL; PROPYLENE GLYCOL; .ALPHA.-TOCOPHEROL ACETATE

DISINFECTING WIPES

DISINFECTING WIPES

Active Ingredient(s)

BENZALKONIUM CHLORIDE 0.0052mg/pcs. Purpose: Antiseptic

Purpose

Antiseptic, DISINFECTING WIPES

Use

DISINFECTING WIPES to help reduce bacteria that potentially can cause disease. For use when soap and water are not available.

Warnings

For external use only. Flammable. Keep away from heat or flame

Do not use

- in children less than 2 months of age
- on open skin wounds

When using this product keep out of eyes, ears, and mouth. In case of contact with eyes, rinse eyes thoroughly with water.
Stop use and ask a doctor if irritation or rash occurs. These may be signs of a serious condition.
Keep out of reach of children. If swallowed, get medical help or contact a Poison Control Center right away.

Stop use and ask a doctor if irritation or rash occurs. These may be signs of a serious condition.

Keep out of reach of children. If swallowed, get medical help or contact a Poison Control Center right away.

Directions

- Wet hands thoroghly with product and allow to dry.
- Discard wipes in trash receptacle after use. Do not flush.
- Supervise children under 6 years of age when using this product to avoid swallowing.

Other information

- Store between 15-30C (59-86F)
- Avoid freezing and excessive heat above 40C (104F)

Inactive ingredients

Aloe Barbadensis Leaf Juice
Fragrance
Phenoxyethanol
Polysorbate 20
Propylene Glycol
Tocopheryl Acetata
Water